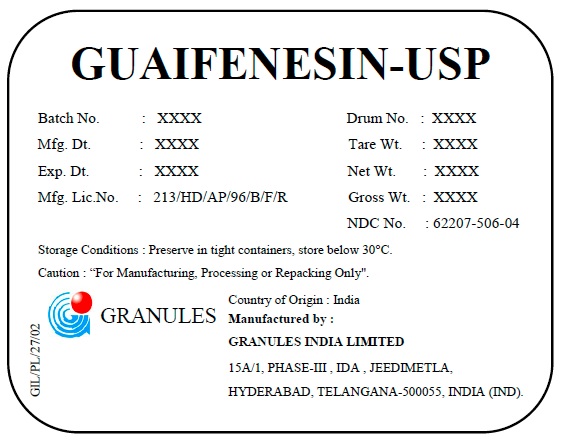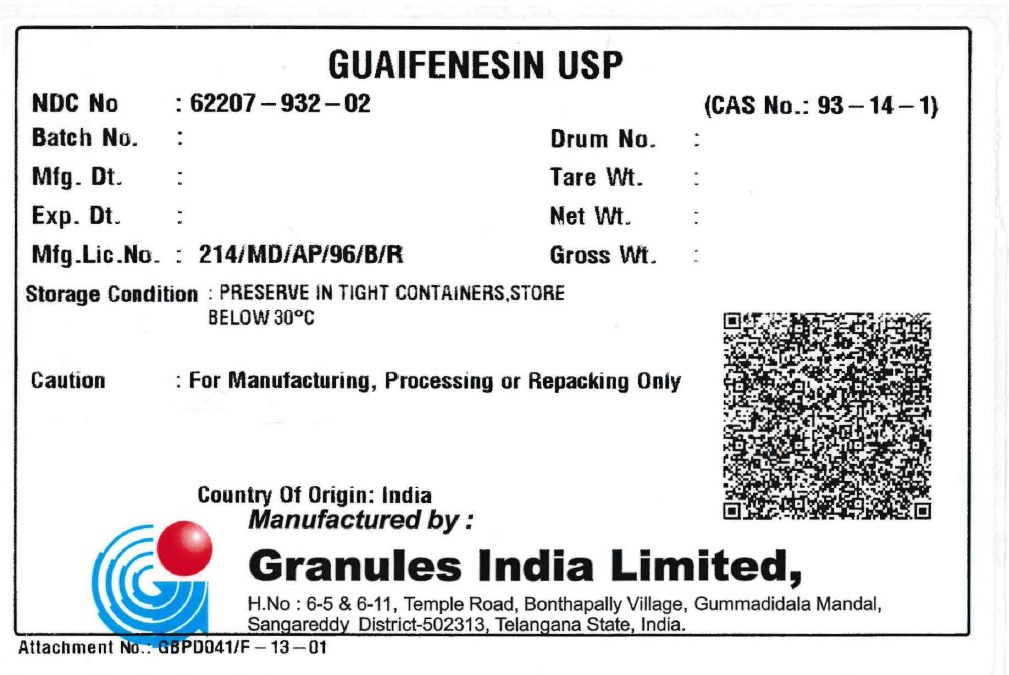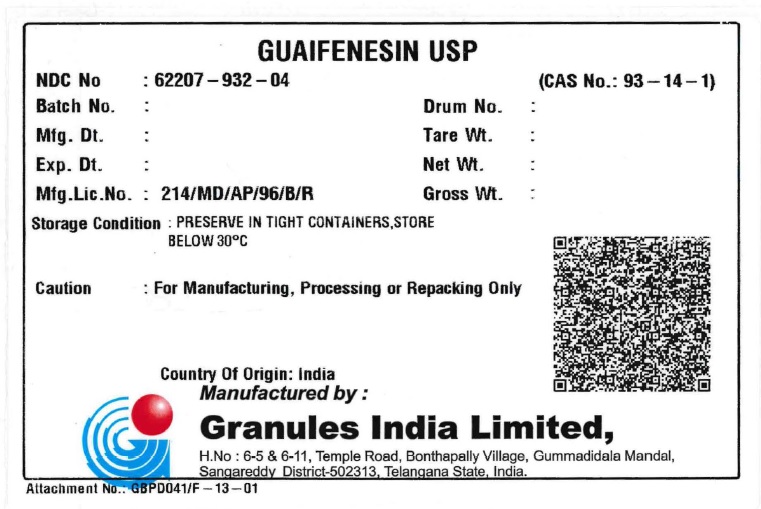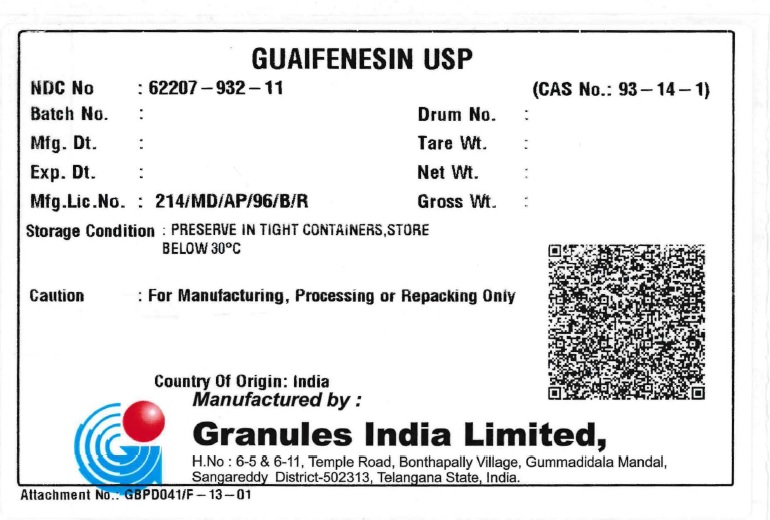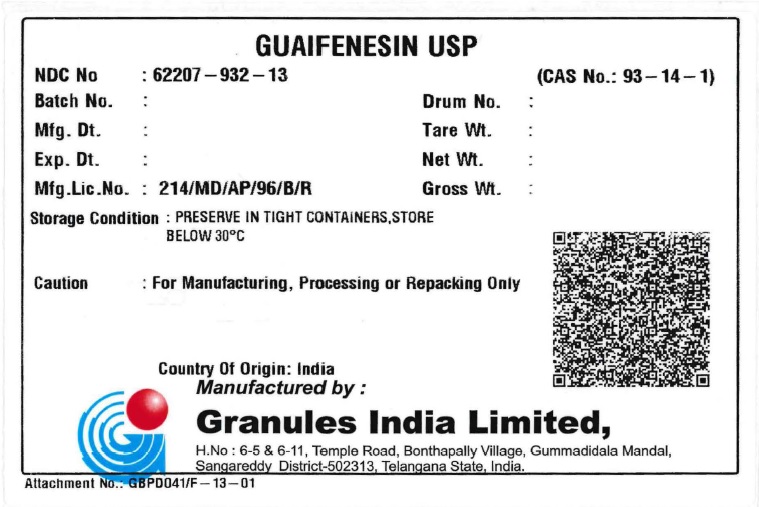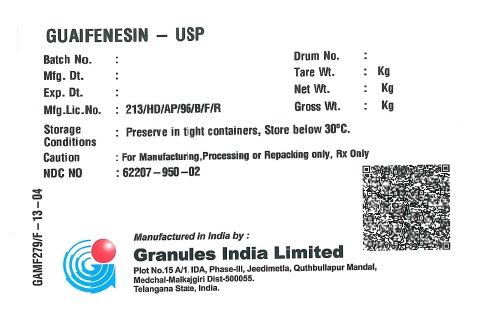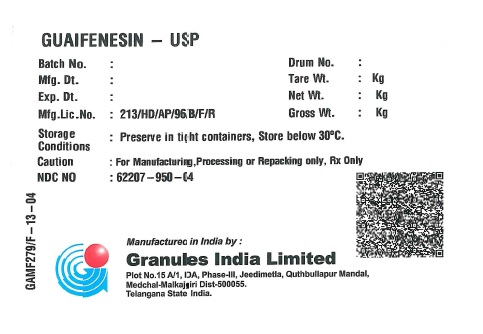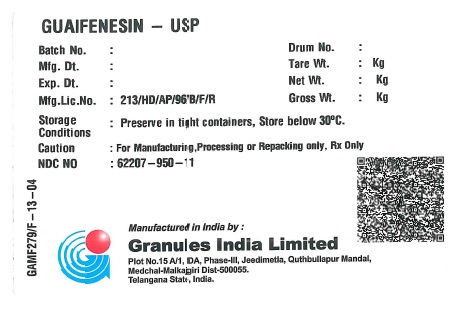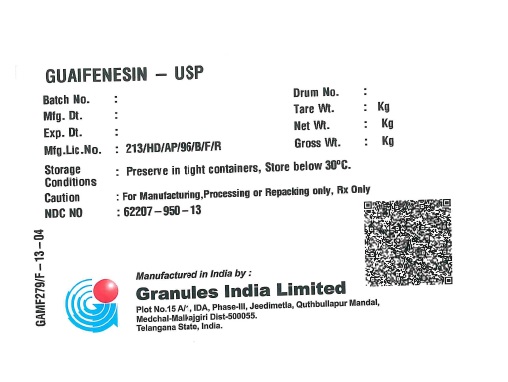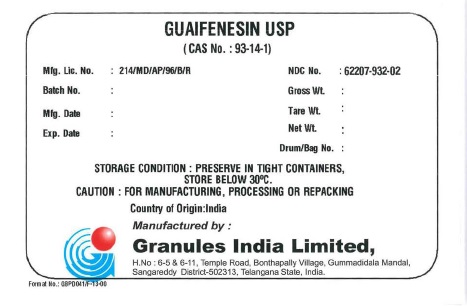 DRUG LABEL: Guaifenesin
NDC: 62207-932 | Form: POWDER
Manufacturer: Granules India Limited
Category: other | Type: BULK INGREDIENT
Date: 20251024

ACTIVE INGREDIENTS: GUAIFENESIN 1 kg/1 kg

GUAIFENESIN – USP